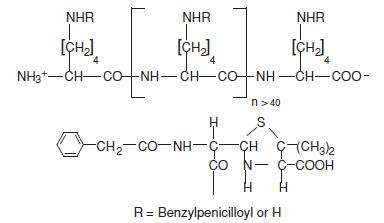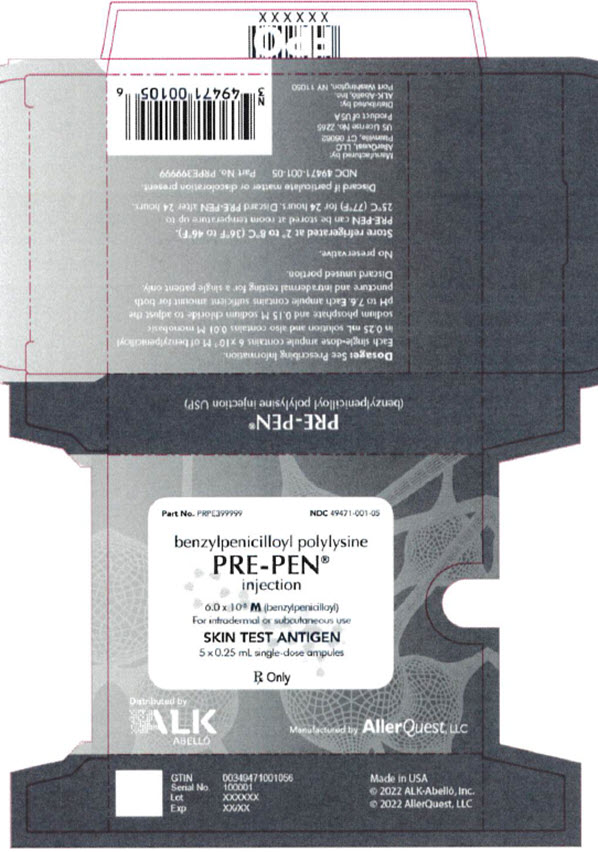 DRUG LABEL: PRE-PEN
NDC: 49471-001 | Form: INJECTION
Manufacturer: AllerQuest LLC
Category: prescription | Type: HUMAN PRESCRIPTION DRUG LABEL
Date: 20240112

ACTIVE INGREDIENTS: BENZYLPENICILLOYL POLYLYSINE 60 umol/0.25 mL
INACTIVE INGREDIENTS: SODIUM CHLORIDE; SODIUM PHOSPHATE, MONOBASIC, UNSPECIFIED FORM; SODIUM PHOSPHATE, DIBASIC, ANHYDROUS; WATER

PRE-PEN® (benzylpenicilloyl polylysine) injection
Skin Test Antigen

DESCRIPTION:

PRE-PEN® (benzylpenicilloyl polylysine) injection is a sterile solution of benzylpenicilloyl polylysine in a concentration of 6.0 X 10^-5M (benzylpenicilloyl) in 0.01 M monobasic sodium phosphate and 0.15 M sodium chloride. Benzylpenicilloyl polylysine is a derivative of poly-l-lysine, where the epsilon amino groups are substituted with benzylpenicilloyl groups (50-70%) forming benzylpenicilloyl alpha amide. Each single-dose ampule contains 0.25 mL of PRE-PEN.

PRE-PEN has the following structure:

CLINICAL PHARMACOLOGY:

PRE-PEN is a skin test antigen reagent that reacts specifically with benzylpenicilloyl IgE antibodies initiating the release of chemical mediators which produce an immediate wheal and flare reaction at a skin test site. All individuals exhibiting a positive skin test to PRE-PEN possess IgE against the benzylpenicilloyl structural group which is a hapten. A hapten is a low molecular weight chemical that conjugates with a carrier (e.g. poly-l-lysine) resulting in the formation of an antigen with the hapten’s specificity. The benzylpenicilloyl hapten is the major antigenic determinant in penicillin-allergic individuals. However, many individuals reacting positively to PRE-PEN will not develop a systemic allergic reaction on subsequent exposure to therapeutic penicillin, especially among those who have not reacted to penicillins in the past. Thus, the PRE-PEN skin test determines the presence of penicilloyl IgE antibodies which are necessary but not sufficient for acute allergic reactions due to the major penicilloyl determinant.

Non-benzylpenicilloyl haptens are designated as minor determinants, since they less frequently elicit an immune response in penicillin treated individuals. The minor determinants may nevertheless be associated with significant clinical hypersensitivity. PRE-PEN does not react with IgE antibodies directed against non-benzylpenicilloyl haptens.

INDICATIONS AND USAGE:

PRE-PEN is indicated for the assessment of sensitization to penicillin (benzylpenicillin or penicillin G) in patients suspected to have clinical penicillin hypersensitivity. A negative skin test to PRE-PEN is associated with an incidence of immediate allergic reactions of less than 5% after the administration of therapeutic penicillin, whereas the incidence may be more than 50% in a history-positive patient with a positive skin test to PRE-PEN. These allergic reactions are predominantly dermatologic. Whether a negative skin test to PRE-PEN predicts a lower risk of anaphylaxis is not established. Similarly, when deciding the risk of proposed penicillin treatment, there are not enough data at present to permit relative weighing in individual cases of a history of clinical penicillin hypersensitivity as compared to positive skin tests to PRE-PEN and/or minor penicillin determinants.

CONTRAINDICATIONS:

PRE-PEN is contraindicated in those patients who have exhibited either a systemic or marked local reaction to its previous administration. Patients known to be extremely hypersensitive to penicillin should not be skin tested.

WARNINGS:

The risk of sensitization to repeated skin testing with PRE-PEN is not established. Rarely, a systemic allergic reaction including anaphylaxis (see below) may follow a skin test with PRE-PEN. To decrease the risk of a systemic allergic reaction, puncture skin testing should be performed first. Intradermal skin testing should be performed only if the puncture test is entirely negative.

PRECAUTIONS:

General:

No reagent, test, or combination of tests will completely assure that a reaction to penicillin therapy will not occur.

The value of the PRE-PEN skin test alone as a means of assessing the risk of administering therapeutic penicillin (when penicillin is the preferred drug of choice) in the following situations is not established:

1. Adult patients who give no history of clinical penicillin hypersensitivity.
2. Pediatric patients.

In addition, the clinical value of PRE-PEN where exposure to penicillin is suspected as a cause of a current drug reaction or in patients who are undergoing routine allergy evaluation is not known. Likewise, the clinical value of PRE-PEN skin tests alone in determining the risk of administering semi-synthetic penicillins (phenoxymethyl penicillin, ampicillin, carbenicillin, dicloxacillin, methicillin, nafcillin, oxacillin, amoxicillin), cephalosporin-derived antibiotics, and penem antibiotics is not known.

In addition to the results of the PRE-PEN skin test, the decision to administer or not administer penicillin should take into account individual patient factors. Healthcare professionals should keep in mind the following:

1. A serious allergic reaction to therapeutic penicillin may occur in a patient with a negative skin test to PRE-PEN.
2. It is possible for a patient to have an anaphylactic reaction to therapeutic penicillin in the presence of a negative PRE-PEN skin test and a negative history of clinical penicillin hypersensitivity.
3. If penicillin is the drug of choice for a life-threatening infection, successful desensitization with therapeutic penicillin may be possible irrespective of a positive skin test and/or a positive history of clinical penicillin hypersensitivity.

Pregnancy:

Animal reproduction studies have not been conducted with PRE-PEN. It is not known whether PRE-PEN can cause fetal harm when administered to a pregnant woman or can affect reproduction capacity. The hazards of skin testing in such patients should be weighed against the hazard of penicillin therapy without skin testing.

ADVERSE REACTIONS:

Occasionally, patients may develop an intense local inflammatory response at the skin test site. Rarely, patients will develop a systemic allergic reaction, manifested by generalized erythema, pruritus, angioedema, urticaria, dyspnea, hypotension, and anaphylaxis. The usual methods of treating a skin test antigen-induced reaction — the applications of a venous occlusion tourniquet proximal to the skin test site and administration of epinephrine are recommended. The patient should be kept under observation for several hours.

DOSAGE AND ADMINISTRATION:

SKIN TESTING DOSAGE AND TECHNIQUE

Skin testing responses can be attenuated by interfering drugs (e.g. H1-antihistamines and vasopressors). Skin testing should be delayed until the effects of such drugs have dissipated, or a separate skin test with histamine can be used to evaluate persistent antihistaminic effects in vivo. Due to the risk of potential systemic allergic reactions, skin testing should be performed in an appropriate healthcare setting under direct medical supervision.

Puncture Testing:

Skin testing is usually performed on the inner volar aspect of the forearm. The skin test antigen should always be applied first by the puncture technique. After preparing the skin surface, apply a small drop of PRE-PEN solution using a sterile 22-28 gauge needle. The same needle can then be used to make a single shallow puncture of the epidermis through the drop of PRE-PEN. Very little pressure is required to break the epidermal continuity. Observe for the appearance of a wheal, erythema, and the occurrence of itching at the test site during the succeeding 15 minutes at which time the solution over the puncture site is wiped off. A positive reaction consists of the development within 10 minutes of a pale wheal, sometimes with pseudopods, surrounding the puncture site and varying in diameter from 5 to 15 mm (or more). This wheal may be surrounded by a variable diameter of erythema, and accompanied by a variable degree of itching. The most sensitive individuals develop itching quickly, and the wheal and erythema are prompt in their appearance. As soon as a positive response as defined above is clearly evident, the solution over the scratch should be immediately wiped off. If the puncture test is either negative or equivocally positive (less than 5 mm wheal with little or no erythema and no itching), an intradermal test may be performed.

The lntradermal Test:

Using a 0.5 to 1.0 cc syringe with a 3/8” to 5/8”long, 26 to 30 gauge, short bevel needle, withdraw the contents of the ampule. Prepare with an alcohol swab a skin test area on the upper, outer arm, sufficiently below the deltoid muscle to permit proximal application of a tourniquet later, if necessary. Be sure to eject all air from the syringe through the needle, then insert the needle, bevel up immediately below the skin surface. Inject an amount of PRE-PEN sufficient to raise a small intradermal bleb of about 3 mm in diameter, in duplicate at least 2 cm apart. Using a separate syringe and needle, inject a like amount of saline or allergen diluting solution as a control at least 5 cm removed from the antigen test sites. Most skin reactions will develop within 5-15 minutes and response to the skin test is read at 20 minutes as follows:

Negative response — no increase in size of original bleb and no greater reaction than the control site.

Ambiguous response — wheal only slightly larger than initial injection bleb, with or without accompanying erythematous flare and slightly larger than the control site; OR discordance between duplicates.

Positive response — itching and significant increase in size of original blebs to at least 5 mm. Wheal may exceed 20 mm in diameter and exhibit pseudopods.

If the control site exhibits a wheal greater than 2-3 mm, repeat the test, and if the same reaction is observed, a physician experienced with allergy skin testing should be consulted.

HOW SUPPLIED: NDC 49471-001-05

PRE-PEN® (benzylpenicilloyl polylysine) injection is a clear, colorless, sterile solution in a concentration of 6.0 X 10^-5M (benzylpenicilloyl) supplied in ampules containing 0.25 mL.

Box of 5 single-dose ampules. Ampules are opened by snapping the neck of the ampule using two forefingers of each hand. Visually inspect for glass shards before use. Each ampule is for single patient use only. Discard any unused portion.

Store PRE-PEN refrigerated at 2°C to 8°C (36°F to 46°F). If removed from refrigerator, PRE-PEN should be kept at room temperature up to 25°C (77°F) and must be used within 24 hours. Discard any unused portion. As with all parenteral drug products, PRE-PEN should be inspected visually for particulate matter and discoloration prior to administration. Report presence of particulate matter or discoloration to Manufacturer.

Rx only

Manufactured by
AllerQuest LLC
10 Farmington Valley Drive, Suite 106, Plainville, CT 06062

US License No. 2265

Distributed by
ALK-Abelló, Inc.
35 Channel Drive, Port Washington, NY 11050

Printed in USA

PRPE399999 12/2022
©2022 ALK-Abelló, Inc. and AllerQuest LLC

PRINCIPAL DISPLAY PANEL - Carton Label

Carton Label

Part No. PRPE399999 NDC 49471-001-05

benzylpenicilloyl polylysine
Pre-Pen®
injection

6.0 x 10^-5 M (benzylpenicilloyl)
For intradermal or subcutaneous use

SKIN TEST ANTIGEN

5 x 0.25 mL single-dose ampules

Rx Only

Distributed by
ALK-ABELLÓ

Manufactured by Aller Quest, LLC

GTIN 00349471001056
Serial No. 100001
Lot XXXXXX
Exp XX/XX

Made in USA
© 2022 ALK-Abelló, Inc.
© 2022 AllerQuest, LLC

Dosage: See Prescribing information.
Each single-dose ampule contains 6 x 10^-5 M of benzylpenicilloyl
in 0.25 mL solution and also contains 0.01 M monobasic
sodium phosphate and 0.15 M sodium chloride to adjust the
ph to 7.6. Each ampule contains sufficient amount for both
puncture and intradermal testing for a single patient only
Discard unused portion

No preservative

Store refrigerated at 2° to 8°C (36°F to 46°F).
PRE-PEN can be stored at room temperature up to
25°C (77°F) for 24 hours. Discard PRE-PEN after 24 hours.

Discard if particulate matter or discoloration present.

NDC 49471-001-05 Part No. PRPE399999

Manufactured by:
AllerQuest, LLC
Plainville, CT 06062

US License No. 2265
Product of USA

Distributed by:
ALK-Abelló, Inc.
Port Washington, NY 11050